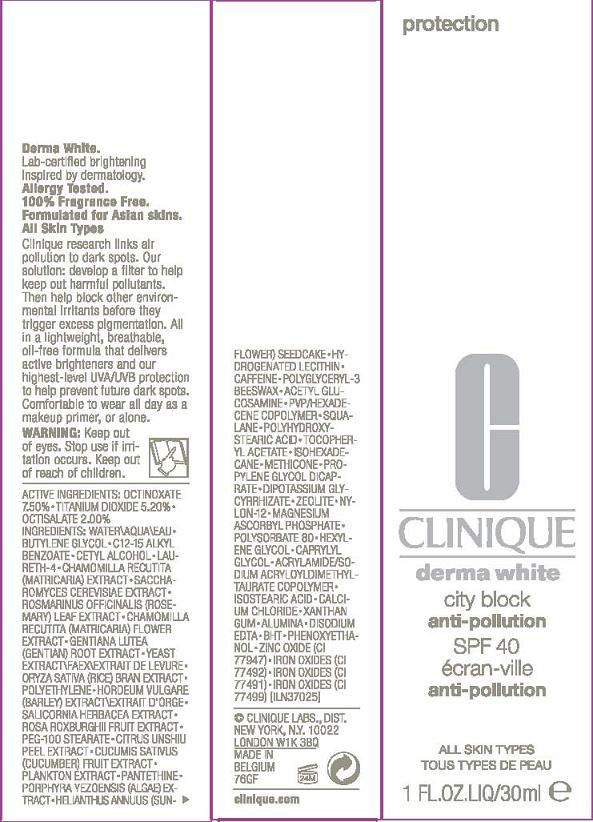 DRUG LABEL: DERMA WHITE
NDC: 49527-008 | Form: CREAM
Manufacturer: CLINIQUE LABS INC
Category: otc | Type: HUMAN OTC DRUG LABEL
Date: 20110211

ACTIVE INGREDIENTS: OCTINOXATE 7.5 mL/100 mL; TITANIUM DIOXIDE 5.2 mL/100 mL; OCTISALATE 2.0 mL/100 mL
INACTIVE INGREDIENTS: WATER; BUTYLENE GLYCOL; CETYL ALCOHOL; CHAMAEMELUM NOBILE; HIGH DENSITY POLYETHYLENE; LECITHIN, SOYBEAN; SQUALANE; .ALPHA.-TOCOPHEROL ACETATE, DL- ; POLYSORBATE 20

ACTIVE INGREDIENT

active ingredients: octinoxate 7.50% [] titanium dioxide 5.20% [] octisalate 2.00%

INACTIVE INGREDIENT

inactive ingredients: water [] butylene glycol [] c12-15 alkyl benzoate [] cetyl alcohol [] laureth-4 [] chamomilla recutita (matricaria) extract [] saccharomyces cerevisiae extract [] rosmarinus officinalis (rosemary) leaf extract [] chamomilla recutita (matricaria) flower extract [] gentiana lutea (gentian) root extract [] yeast extract\faex\extrait de levure [] oryza sativa (rice) bran extract [] polyethylene [] hordeum vulgare (barley) extract\extrait d'orge [] salicornia herbacea extract [] rosa roxburghii fruit extract [] peg-100 stearate [] citrus unshiu peel extract [] cucumis sativus (cucumber) fruit extract [] plankton extract [] pantethine [] porphyra yezoensis (algae) extract [] helianthus annuus (sunflower) seedcake [] hydrogenated lecithin [] caffeine [] polyglyceryl-3 beeswax [] acetyl glucosamine [] pvp/hexadecene copolymer [] squalane [] polyhydroxystearic acid [] tocopheryl acetate [] isohexadecane [] methicone [] propylene glycol dicaprate [] dipotassium glycyrrhizate [] zeolite [] nylon-12 [] magnesium ascorbyl phosphate [] polysorbate 80 [] hexylene glycol [] caprylyl glycol [] acrylamide/sodium acryloyldimethyltaurate copolymer [] isostearic acid [] calcium chloride [] xanthan gum [] alumina [] disodium edta [] bht [] phenoxyethanol [] zinc oxide (ci 77947) [] iron oxides (ci 77491, ci 77492, ci 77499)

WARNINGS

warning: keep out of eyes. stop use if irritation occurs.

keep out of reach of children.

PACKAGE LABEL

PRINCIPAL DISPLAY PANEL:

CLINIQUE
DERMA WHITE
CITY BLOCK
ANTI-POLLUTION SPF 40
ALL SKIN TYPES
1 FL OZ LIQ / 30 ML
CLINIQUE LABS DISTR.
NEW YORK, NY 10022